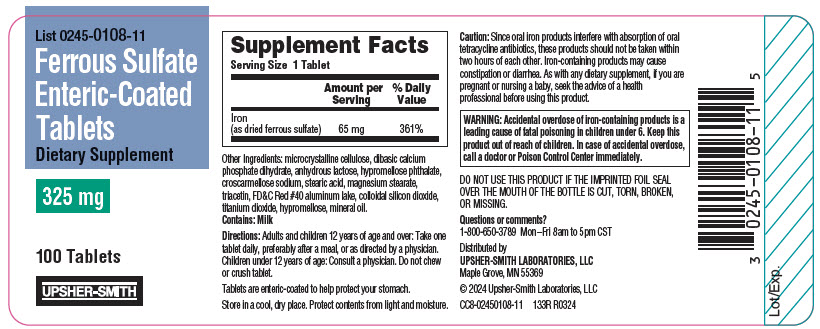 DRUG LABEL: Ferrous Sulfate
NDC: 0245-0108 | Form: TABLET
Manufacturer: Upsher-Smith Laboratories. LLC
Category: other | Type: DIETARY SUPPLEMENT
Date: 20240415

ACTIVE INGREDIENTS: Ferrous Sulfate 65 mg/1 1
INACTIVE INGREDIENTS: MICROCRYSTALLINE CELLULOSE; DIBASIC CALCIUM PHOSPHATE DIHYDRATE; ANHYDROUS LACTOSE; HYPROMELLOSE PHTHALATE (24% PHTHALATE, 55 CST); CROSCARMELLOSE SODIUM; STEARIC ACID; MAGNESIUM STEARATE; FD&C RED NO. 40; SILICON DIOXIDE; TITANIUM DIOXIDE; HYPROMELLOSE, UNSPECIFIED; MINERAL OIL

Ferrous Sulfate Enteric-Coated Tablets

STATEMENT OF IDENTITY

Supplement Facts
Serving Size 1 Tablet
 | Amount per Serving | % Daily Value
Iron (as dried ferrous sulfate) | 65 mg | 361%

Other Ingredients: microcrystalline cellulose, dibasic calcium phosphate dihydrate, anhydrous lactose, hypromellose phthalate, croscarmellose sodium, stearic acid, magnesium stearate, triacetin, FD&C Red #40 aluminum lake, colloidal silicon dioxide, titanium dioxide, hypromellose, mineral oil.

Contains: Milk

Directions

Adults and children 12 years of age and over: Take one tablet daily, preferably after a meal, or as directed by a physician. Children under 12 years of age: Consult a physician. Do not chew or crush tablet.

Tablets are enteric-coated to help protect your stomach.

SAFE HANDLING WARNING

Store in a cool, dry place. Protect contents from light and moisture.

Caution

Since oral iron products interfere with absorption of oral tetracycline antibiotics, these products should not be taken within two hours of each other. Iron-containing products may cause constipation or diarrhea. As with any dietary supplement, if you are pregnant or nursing a baby, seek the advice of a health professional before using this product.

WARNINGS

WARNING: Accidental overdose of iron-containing products is a leading cause of fatal poisoning in children under 6. Keep this product out of reach of children. In case of accidental overdose, call a doctor or Poison Control Center immediately.

DO NOT USE THIS PRODUCT IF THE IMPRINTED FOIL SEAL OVER THE MOUTH OF THE BOTTLE IS CUT, TORN, BROKEN, OR MISSING.

Questions or comments?

1-800-650-3789 Mon–Fri 8am to 5pm CST

HEALTH CLAIM

Distributed by
UPSHER-SMITH LABORATORIES, LLC
Maple Grove, MN 55369

© 2024 Upsher-Smith Laboratories, LLC

CC8-02450108-11
133R R0324

PRINCIPAL DISPLAY PANEL - 325 mg Blister Pack Label

List 0245-0108-11

Ferrous Sulfate
Enteric-Coated
Tablets

Dietary Supplement

325 mg

100 Tablets

UPSHER-SMITH